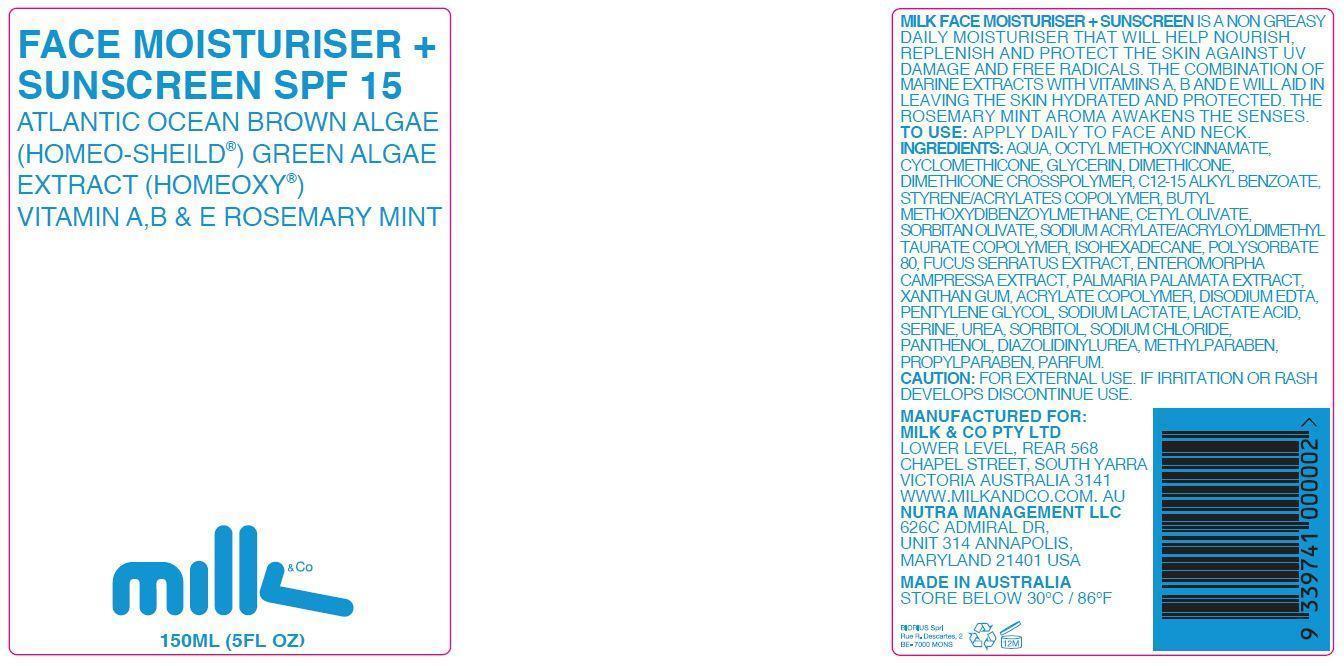 DRUG LABEL: Face Moisturiser
NDC: 61671-004 | Form: LOTION
Manufacturer: Milk & Co Pty Ltd
Category: otc | Type: HUMAN OTC DRUG LABEL
Date: 20140108

ACTIVE INGREDIENTS: AVOBENZONE 3 g/150 g; OCTINOXATE 7 g/150 g
INACTIVE INGREDIENTS: WATER; ALKYL (C12-15) BENZOATE; CETEARYL OLIVATE; CYCLOMETHICONE; DIAZOLIDINYL UREA; DIMETHICONE; EDETATE DISODIUM; ULVA COMPRESSA; FUCUS SERRATUS; GLYCERIN; ISOHEXADECANE; LACTIC ACID; METHYLPARABEN; DULSE; PANTHENOL; PENTYLENE GLYCOL; POLYSORBATE 80; PROPYLPARABEN; SERINE; SODIUM CHLORIDE; SODIUM LACTATE; SORBITAN OLIVATE; SORBITOL; METHACRYLATE/METHOXY PEG-10 MALEATE/STYRENE COPOLYMER; UREA; XANTHAN GUM; SODIUM ACRYLATE/SODIUM ACRYLOYLDIMETHYLTAURATE COPOLYMER (4000000 MW)

ACTIVE INGREDIENT

Avobenzone and Octinoxate

PURPOSE

Face Moisturiser + Sunscreen SPF 15

Atlantic Ocean Brown Algae

(Homeo-Sheild®) Green Algae Extract (Homeoxy®)

Vitamin A, B & E Rosemary Mint

Milk & co

150 ML (5 FL OZ)

Keep out of reach of children

INDICATIONS AND USAGE

Milk Face Moisturiser + Sunscreen is a non greasy daily moisturiser that will help nourish, replenish and protect the skin against UV damage and free radicals. The combination of marine extracts with vitamins A, B and E will aid in leaving the skin hydrated and protected. The rosemary mint aroma awakens the senses.

WARNINGS

Caution: for external use. If irritation or rash develops discontinue use.

DOSAGE AND ADMINISTRATION

To use: apply daily to face and neck.

INACTIVE INGREDIENT

Ingredients: aqua, octyl methoxycinnamate, cyclomethicone, glycerin, dimethicone, dimethicone crosspolymer, c12-15 alkyl benzoate, styrene/acrylates copolymer, butyl methoxydibenzoylmethane, cetyl olivate, sorbitan olivate, sodium acrylate/acryloyldimethyl taurate copolymer, isohexadecane, polysorbate 80, fucus serratus extract, enteromorpha campressa extract, palmaria palamata extract, xanthan gum, acrylate copolymer, disodium EDTA, pentylene glycol, sodium lactate, lactate acid, serine, urea, sorbitol, sodium chloride, panthenol, diazolidinylurea, methylparaben, propylparaben, parfum.

OTHER SAFETY INFORMATION

Manufactured for:

Milk & Co Pty Ltd

Lower Level, Rear 568

Chapel Street, South Yarra

Victoria Australia 3141

www.milkandco.com.au

Nutra Management LLC

626C Admiral Dr.

Unite 314 Annapolis,

Maryland 21401 USA

Made in Australia

Store below 30oC / 86oF